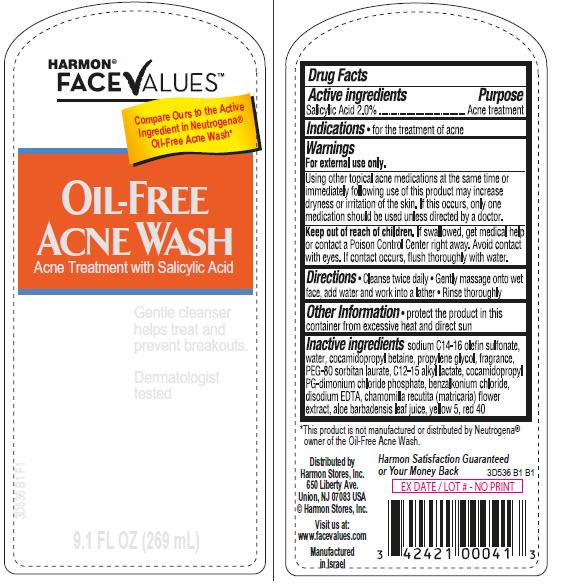 DRUG LABEL: Oil-Free Acne Wash
NDC: 63940-536 | Form: SOLUTION
Manufacturer: Harmon Stores Inc
Category: otc | Type: HUMAN OTC DRUG LABEL
Date: 20131112

ACTIVE INGREDIENTS: SALICYLIC ACID 2 g/100 mL
INACTIVE INGREDIENTS: SODIUM C14-16 OLEFIN SULFONATE; WATER; COCAMIDOPROPYL BETAINE; PROPYLENE GLYCOL; SORBITAN MONOLAURATE; C12-15 ALKYL LACTATE; COCAMIDOPROPYL PG-DIMONIUM CHLORIDE PHOSPHATE; BENZALKONIUM CHLORIDE; EDETATE DISODIUM; CHAMOMILE; ALOE VERA LEAF; FD&C YELLOW NO. 5; FD&C RED NO. 40

Harmon® Face Values Oil-Free Acne Wash

Active ingredient

Salicylic Acid 2.0%

Purpose

Acne Treatment

Indications

- for the treatment of acne

Warnings

For external use only.

Using other topical acne medications at the same time or immediately following use of this product may increase dryness or irritation of the skin. If this occurs, only one medication should be used unless directed by a doctor.

Keep Out of Reach of Children.

If swallowed, get medical help or contact a Poison Control Center right away. Avoid contact with eyes. If contact occurs, flush thoroughly with water.

Directions

- Clean twice daily
- Gently massage onto wet face, add water and work into a lather
- Rinse thoroughly

Other Information

- protect the product in this container from excessive heat and direct sun

Inactive ingredients

sodium C14-16 olefin sulfonate, water, cocamidopropyl betaine, propylene glycol, fragrance, PEG-80 sorbitan laurate, C12-15 alkyl lactate, cocamidopropyl PG-dimonium chloride phosphate, benzalkonium chloride, disodium EDTA, chamomilla recutita (matricaria) flower extract, aloe barbadensis leaf juice, yellow 5, red 40

Package/Label Principal Display Panel

Harmon® FaceValuesTM
Oil-Free Acne Wash
Acne Treatment with Salicylic Acid

Gentle Cleanser helps treat and prevent breakouts

Dermatologist tested

9.1 Fl Oz (269 mL)

Compare Ours to the Active Ingredient in Neutrogena® Oil-Free Acne Wash*

Distributed by

Harmon Stores, Inc.
650 Liberty Ave.
Union, NJ 07083 USA
©Harmon Stores, Inc.

Visit us at:
www.facevalues.com

Manufactured in Israel

Harmon Satisfaction Guaranteed or Your Money Back

3D536 B1 B1

*This product is not manufactured or distributed by Neutrogena® owner of the Oil-Free Acne Wash.

Label